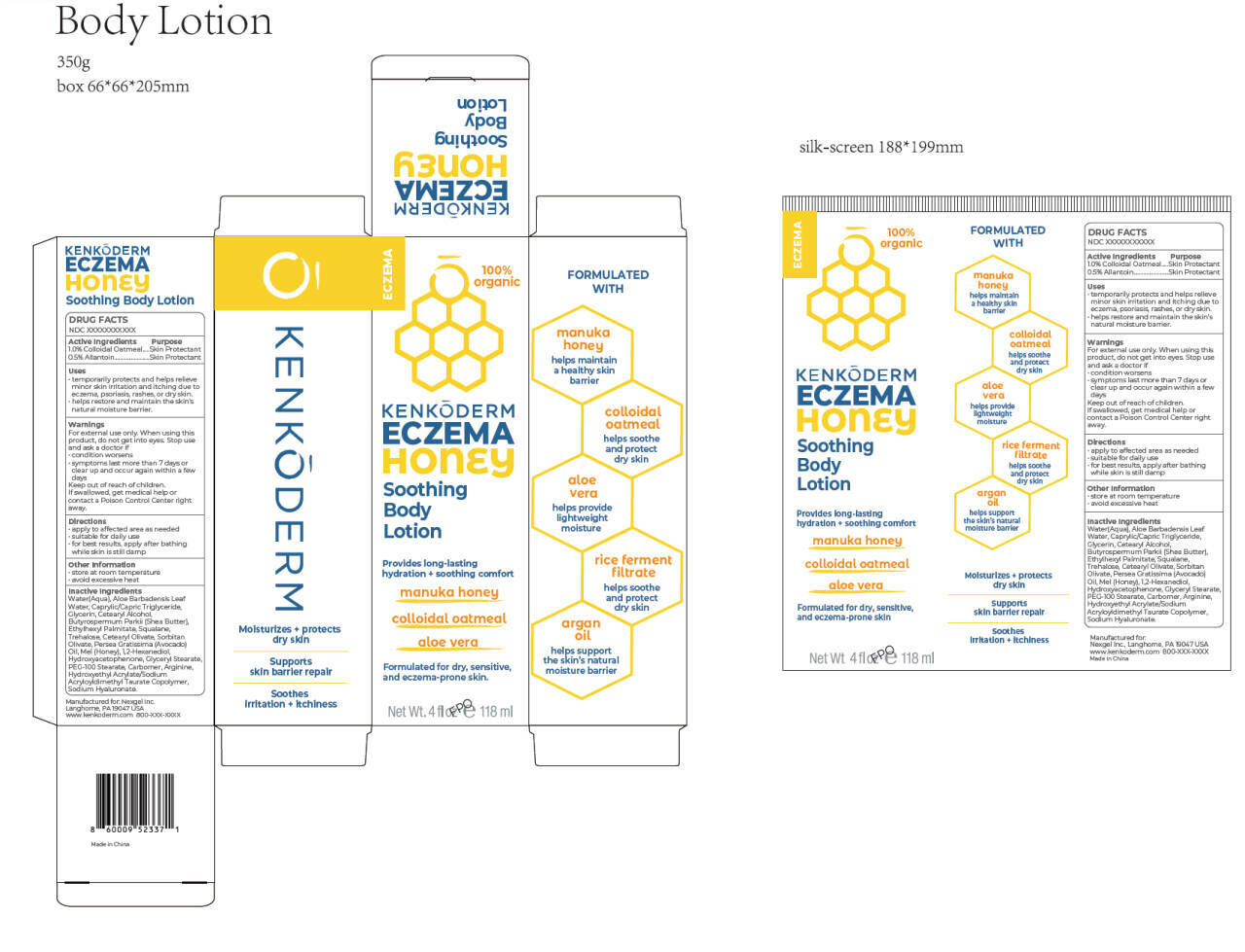 DRUG LABEL: Kenkoderm Eczema Honey Soothing Body
NDC: 84148-019 | Form: CHEWABLE GEL
Manufacturer: Guangzhou Ariel Biotech Co., Ltd.
Category: otc | Type: HUMAN OTC DRUG LABEL
Date: 20260114

ACTIVE INGREDIENTS: ALLANTOIN 0.5 g/100 mL; OATMEAL 1 g/100 mL
INACTIVE INGREDIENTS: ARGININE; PEG-100 STEARATE; CAPRYLIC/CAPRIC TRIGLYCERIDE; WATER; ALOE VERA LEAF OIL; GLYCERIN; CETEARYL ALCOHOL; BUTYROSPERMUM PARKII (SHEA) BUTTER; ETHYLHEXYL PALMITATE; SQUALANE; TREHALOSE; CETEARYL OLIVATE; SORBITAN OLIVATE; PERSEA GRATISSIMA (AVOCADO) OIL; MEL; 1,2-HEXANEDIOL; HYDROXYACETOPHENONE; GLYCERYL STEARATE; CARBOMER; SODIUM HYALURONATE; HYDROXYETHYL ACRYLATE/SODIUM ACRYLOYLDIMETHYL TAURATE COPOLYMER (45000 MPA.S AT 1%)

84148-019

Active Ingredient(s)

1.0% Colloidal Oatmeal

0.5% Allantoin

Purpose

Skin Protectant

Warnings

For external use only.

Do not use on deep or puncture wounds, animal bites, serious burns.

When using this product, do not get into eyes. Stop use and ask a doctor if

• condition worsens
• symptoms last more than 7 days or clear up and occur again within a few days

STOP USE

If swallowed, get medical help or contact a Poison Control Center right away.

Keep out of reach of children.

Other information

• store at room temperature
• avoid excessive heat

Inactive ingredients

Water(Aqua), Aloe Barbadensis Leaf Water, Caprylic/Capric Triglyceride,
Glycerin, Cetearyl Alcohol, Butyrospermum Parkii (Shea Butter),
Ethylhexyl Palmitate, Squalane, Trehalose, Cetearyl Olivate, Sorbitan
Olivate, Persea Gratissima (Avocado) Oil, Mel (Honey), 1,2-Hexanediol,
Hydroxyacetophenone, Glyceryl Stearate, PEG-100 Stearate, Carbomer, Arginine,
Hydroxyethyl Acrylate/Sodium Acryloyldimethyl Taurate Copolymer,
Sodium Hyaluronate.

Use

• temporarily protects and helps relieve
minor skin irritation and itching due to
eczema, psoriasis, rashes, or dry skin.
• helps restore and maintain the skin’s
natural moisture barrier.

Directions

• apply to affected area as needed
• suitable for daily use
• for best results, apply after bathing while skin is still damp